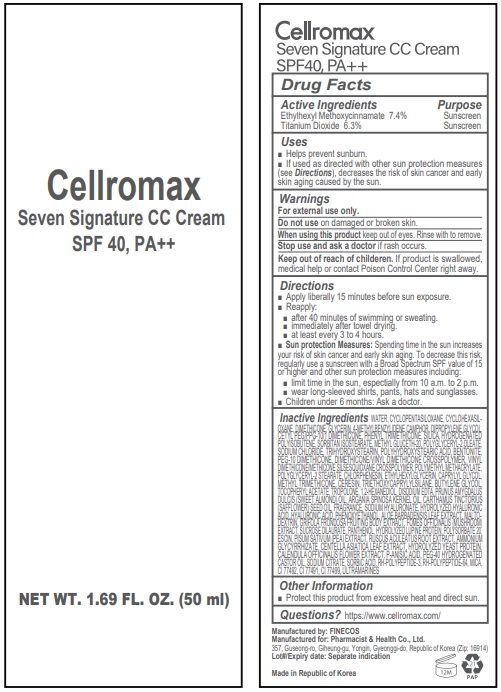 DRUG LABEL: Cellromax 7 Signature CC Cream
NDC: 79895-103 | Form: CREAM
Manufacturer: PHARMACIST&HEALTH CO., LTD.
Category: otc | Type: HUMAN OTC DRUG LABEL
Date: 20201116

ACTIVE INGREDIENTS: TITANIUM DIOXIDE 6.3 g/100 mL; OCTINOXATE 7.4 g/100 mL
INACTIVE INGREDIENTS: GELATIN HYDROLYSATE (PORCINE SKIN, MW 3000); HYDROGENATED POLYBUTENE (1300 MW); CYCLOMETHICONE 6; LARICIFOMES OFFICINALIS FRUITING BODY; TRIHYDROXYSTEARIN; MAITAKE; POLYSORBATE 20; CALENDULA OFFICINALIS FLOWER; EDETATE DISODIUM; POLYHYDROXYSTEARIC ACID (2300 MW); PANTHENOL; SORBIC ACID; FERRIC OXIDE RED; ARGAN OIL; SODIUM CITRATE; DIMETHICONE; SODIUM CHLORIDE; DIMETHICONE/VINYL DIMETHICONE CROSSPOLYMER (SOFT PARTICLE); CHLORPHENESIN; SUCROSE DILAURATE; SILICON DIOXIDE; SAFFLOWER OIL; 1,2-HEXANEDIOL; PHENOXYETHANOL; P-ANISIC ACID; AMMONIUM GLYCYRRHIZATE; POLY(METHYL METHACRYLATE; 450000 MW); CAPRYLYL GLYCOL; RUSCUS ACULEATUS ROOT; ALMOND OIL; POLYGLYCERYL-2 STEARATE; MICA; TROPOLONE; METHYL TRIMETHICONE; BUTYLENE GLYCOL; CERESIN; GLYCERIN; ENZACAMENE; DIPROPYLENE GLYCOL; SORBITAN ISOSTEARATE; METHYL GLUCETH-20; ALOE VERA LEAF; POLYOXYL 40 HYDROGENATED CASTOR OIL; AQUAPORIN-1; CENTELLA ASIATICA LEAF; FERRIC OXIDE YELLOW; PHENYL TRIMETHICONE; CETYL PEG/PPG-10/1 DIMETHICONE (HLB 5); TRIETHOXYCAPRYLYLSILANE; HYALURONIC ACID; FERROSOFERRIC OXIDE; ALPHA-TOCOPHEROL ACETATE; ESCIN; MALTODEXTRIN; PEA; HYALURONATE SODIUM; CYCLOMETHICONE 5; PEG-10 DIMETHICONE (600 CST); ETHYLHEXYLGLYCERIN; POLYGLYCERYL-2 OLEATE; VINYL DIMETHICONE/METHICONE SILSESQUIOXANE CROSSPOLYMER; BENTONITE; ULTRAMARINE VIOLET; FIBROBLAST GROWTH FACTOR 7

ACTIVE INGREDIENT

Ethylhexyl Methoxycinnamate 7.4%, Titanium Dioxide 6.3%

INACTIVE INGREDIENT

Water, Cyclopentasiloxane, Cyclohexasiloxane, Dimethicone, Glycerin, 4-Methylbenzylidene Camphor, Dipropylene Glycol, Cetyl PEG/PPG-10/1 Dimethicone, Phenyl Trimethicone, Silica, Hydrogenated Polyisobutene, Sorbitan Isostearate, Methyl Gluceth-20, Polyglyceryl-2 Oleate, Sodium Chloride, Trihydroxystearin, Polyhydroxystearic Acid, Mica, CI 77492, Bentonite, PEG-10 Dimethicone, Dimethicone/Vinyl Dimethicone Crosspolymer, Vinyl Dimethicone/Methicone Silsesquioxane Crosspolymer, Polymethyl Methacrylate, Polyglyceryl-2 Stearate, Chlorphenesin, Ethylhexylglycerin, Caprylyl Glycol, Methyl Trimethicone, Ceresin, CI 77491, CI 77499, Triethoxycaprylylsilane, Butylene Glycol, Tocopheryl Acetate, Tropolone, Ultramarines, 1,2-Hexanediol, Disodium EDTA, Prunus Amygdalus Dulcis (Sweet Almond) Oil, Argania Spinosa Kernel Oil, Carthamus Tinctorius (Safflower) Seed Oil, Fragrance, Sodium Hyaluronate, Hydrolyzed Hyaluronic Acid, Hyaluronic Acid, Phenoxyethanol, Aloe Barbadensis Leaf Extract, Maltodextrin, Grifola Frondosa Fruiting Body Extract, Fomes Officinalis (Mushroom) Extract, Sucrose Dilaurate, Panthenol, Hydrolyzed Lupine Protein, Polysorbate 20, Escin, Pisum Sativum (Pea) Extract, Ruscus Aculeatus Root Extract, Ammonium Glycyrrhizate, Centella Asiatica Leaf Extract, Hydrolyzed Yeast Protein, Calendula Officinalis Flower Extract, p-Anisic Acid, PEG-40 Hydrogenated Castor Oil, Sodium Citrate, Sorbic Acid, rh-Polypeptide-3, rh-Polypeptide-64

DESCRIPTION

Directions: 1. Apply after basic skin care product. 2. Spread an appropriate amount over the entire face following the skin texture. 3. Reapply as required.

Do not use on damaged or broken Skin. Stop use and ask a doctor if rash occurs.

Keep Out of Reach of Children.

WARNINGS

For external use only.